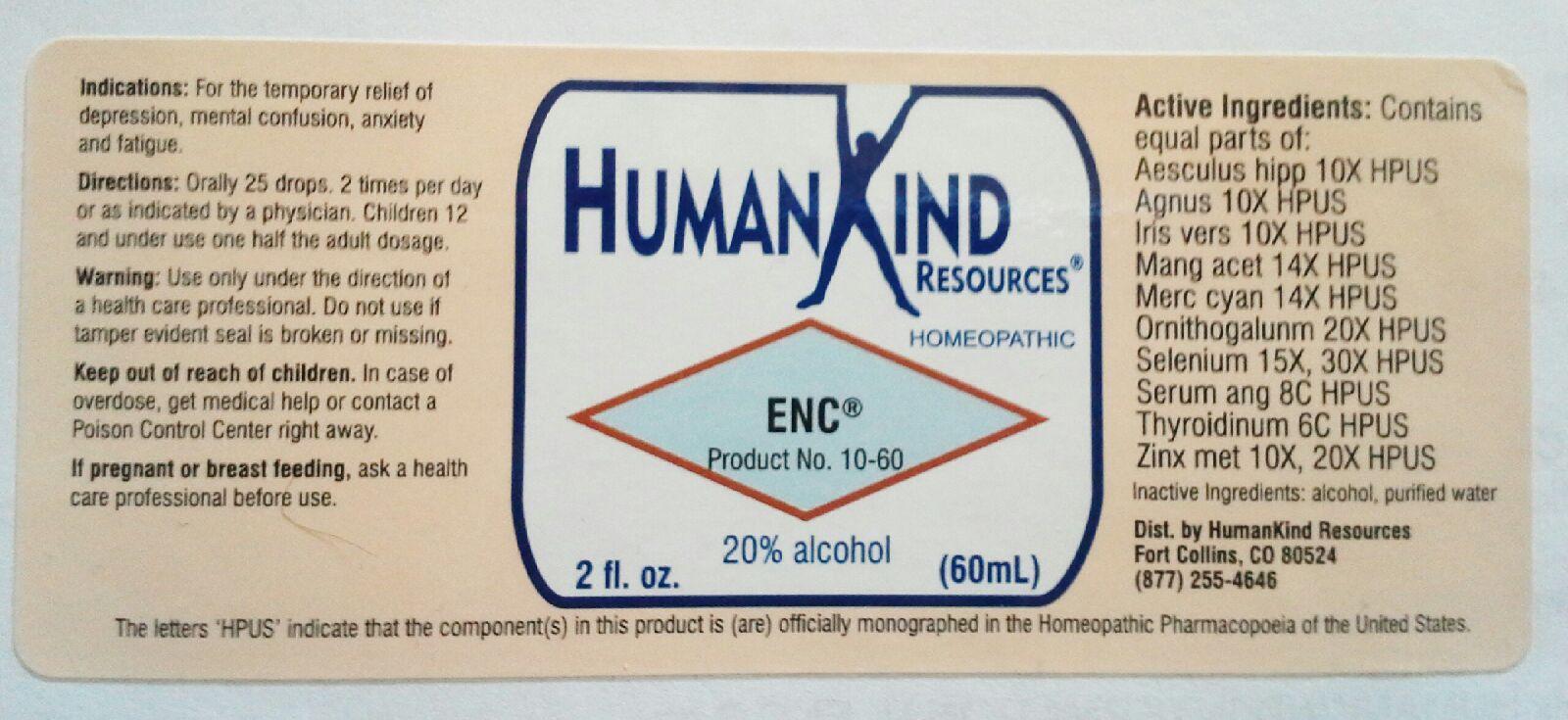 DRUG LABEL: ENC
NDC: 64616-088 | Form: LIQUID
Manufacturer: Vitality Works, Inc.
Category: homeopathic | Type: HUMAN OTC DRUG LABEL
Date: 20251217

ACTIVE INGREDIENTS: HORSE CHESTNUT 10 [hp_X]/1 mL; CHASTE TREE 10 [hp_X]/1 mL; IRIS VERSICOLOR ROOT 10 [hp_X]/1 mL; MANGANESE ACETATE TETRAHYDRATE 14 [hp_X]/1 mL; MERCURIC CYANIDE 14 [hp_X]/1 mL; ORNITHOGALUM UMBELLATUM 20 [hp_X]/1 mL; SELENIUM 30 [hp_X]/1 mL; ANGUILLA ROSTRATA BLOOD SERUM 8 [hp_C]/1 mL; THYROID, UNSPECIFIED 6 [hp_C]/1 mL; ZINC 20 [hp_X]/1 mL
INACTIVE INGREDIENTS: ALCOHOL; WATER

ENC

ENC

Aesulus Hippocastanum 10X Ornithogalum Umbellatum 20X

Agnus Castus 10X Selenium Metallicum 15X, 30X

Iris Versicolor 10X Serum Anguillae 8C

Manganum Aceticum 14X Thyroidinum 6C

Mercurius Cyanatus 14X Zinc Metallicum 10X, 20X

ENC

Alchol, Purified Water

ENC

Use only under the direction of a health care professional. Do not use if tamper evident seal is broken or missing.

ENC

Keep out of the reach of children. In case of overdose, get medical help or contact a Poison Control Center right away.

ENC

For the temporary relief of depression, mental confusion, anxiety and fatigue.

ENC

Orally 25 drops, 2 times per day or as indicated by a physician. Children 12 and under use on half the adult dosage.

ENC

Eases depression, mental confusion, anxiety and fatigue temporarly.